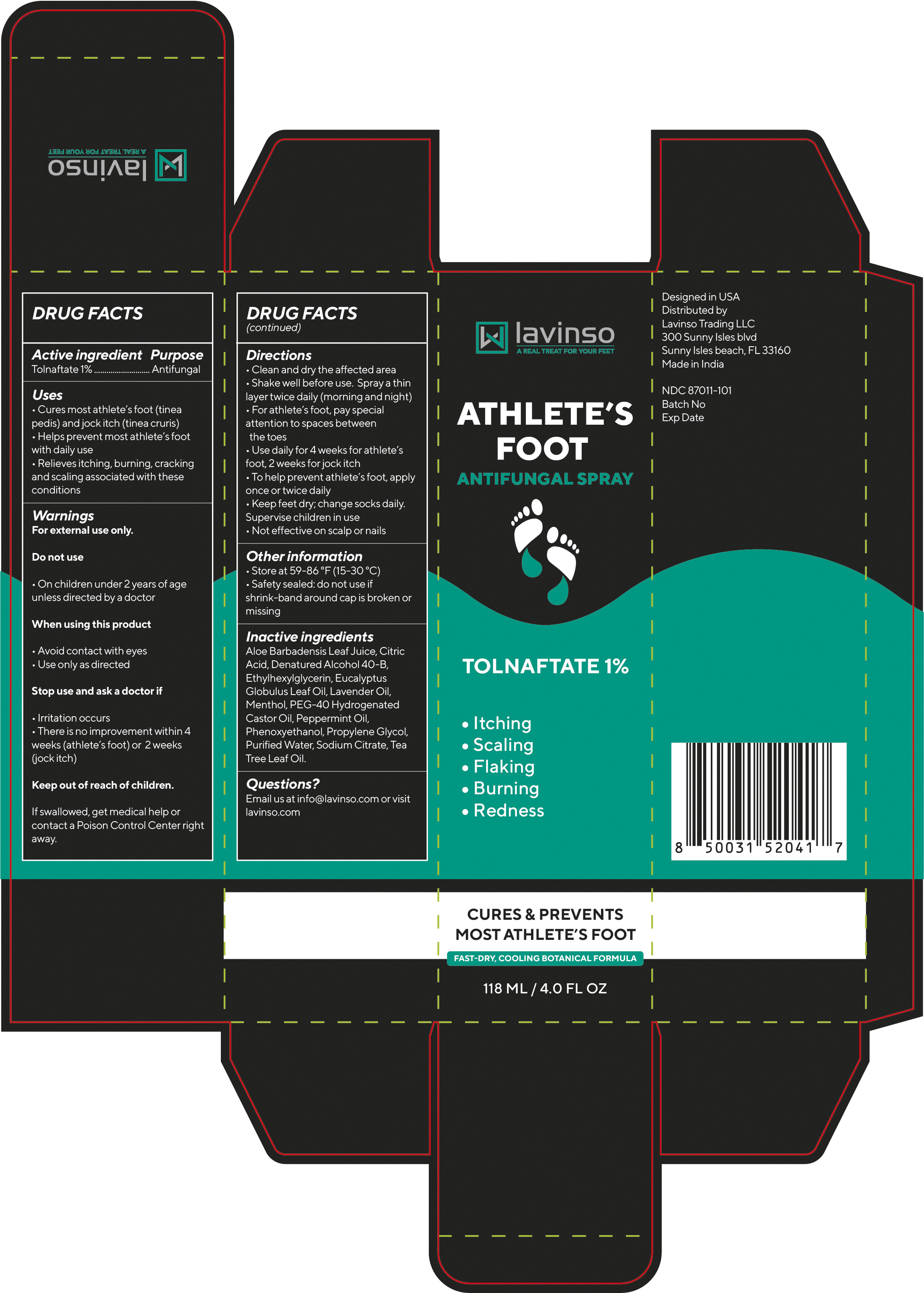 DRUG LABEL: Lavinso Athlete Foot
NDC: 87011-101 | Form: SPRAY
Manufacturer: Lavinso Trading LLC
Category: otc | Type: HUMAN OTC DRUG LABEL
Date: 20250923

ACTIVE INGREDIENTS: TOLNAFTATE 10 mg/1 mL
INACTIVE INGREDIENTS: CITRIC ACID; PHENOXYETHANOL; ETHYLHEXYLGLYCERIN; PEG-40 HYDROGENATED CASTOR OIL; MELALEUCA ALTERNIFOLIA (TEA TREE) LEAF OIL; ALOE BARBADENSIS LEAF JUICE; WATER; SODIUM CITRATE; ALCOHOL; PEPPERMINT OIL; PROPYLENE GLYCOL; EUCALYPTUS GLOBULUS LEAF OIL; LAVENDER OIL; MENTHOL

Lavinso Athlete’s Foot Antifungal Spray – Labeling

Active ingredient
Tolnaftate 1%

Purpose
Antifungal

Uses
• Cures most athlete’s foot (tinea pedis) and jock itch (tinea cruris)
• Helps prevent most athlete’s foot with daily use
• Relieves itching, burning, cracking and scaling associated with these conditions

Warnings
For external use only

Do not use
• On children under 2 years of age unless directed by a doctor

When using this product
• Avoid contact with eyes
• Use only as directed

Stop use and ask a doctor if
• Irritation occurs
• There is no improvement within 4 weeks (athlete’s foot) or 2 weeks (jock itch)

Keep out of reach of children.
If swallowed, get medical help or contact a Poison Control Center right away.

Directions
• Clean and dry the affected area
• Shake well before use. Spray a thin layer twice daily (morning and night)
• For athlete’s foot, pay special attention to spaces between the toes
• Use daily for 4 weeks for athlete’s foot; 2 weeks for jock itch
• To help prevent athlete’s foot, apply once daily
• Keep feet dry; change socks daily. Supervise children in use
• Not effective on scalp or nails

Other information
• Store at 59–86 °F (15–30 °C)
• Safety sealed: do not use if shrink-band around cap is broken or missing

Inactive ingredients
Aloe Barbadensis Leaf Juice, Citric Acid, Denatured Alcohol 40-B, Ethylhexylglycerin, Eucalyptus Globulus Leaf Oil, Lavender Oil, Menthol, PEG-40 Hydrogenated Castor Oil, Peppermint Oil, Phenoxyethanol, Propylene Glycol, Purified Water, Sodium Citrate, Tea Tree Leaf Oil.

Questions?
Email us at info@lavinso.com or visit lavinso.com

When using this product

• Avoid contact with eyes
• Use only as directed

PACKAGE LABEL

ATHLETE’S FOOT
ANTIFUNGAL SPRAY
Tolnaftate 1%
Cures & prevents most athlete’s foot
Fast-dry, cooling botanical formula
118 ML / 4.0 FL OZ

Designed in USA
Distributed by
Lavinso Trading LLC
300 Sunny Isles Blvd, Unit 1204
Sunny Isles Beach, FL 33160 USA

Made in India
NDC 87011-101
Batch No
Exp Date